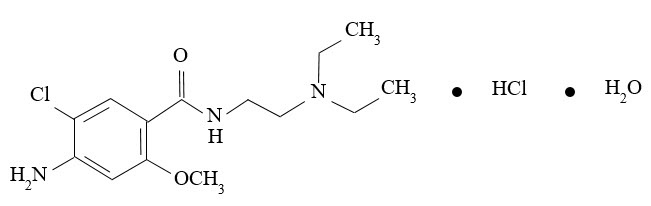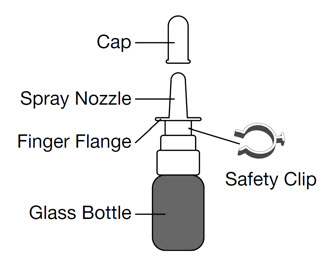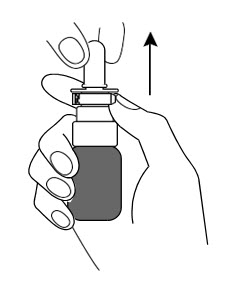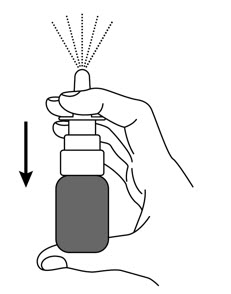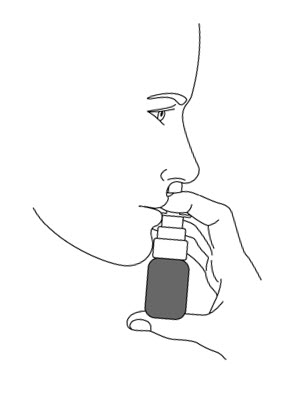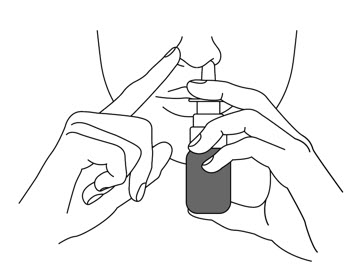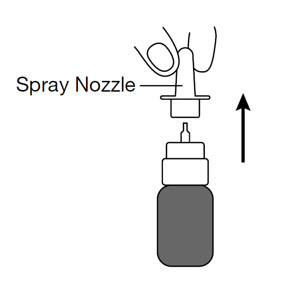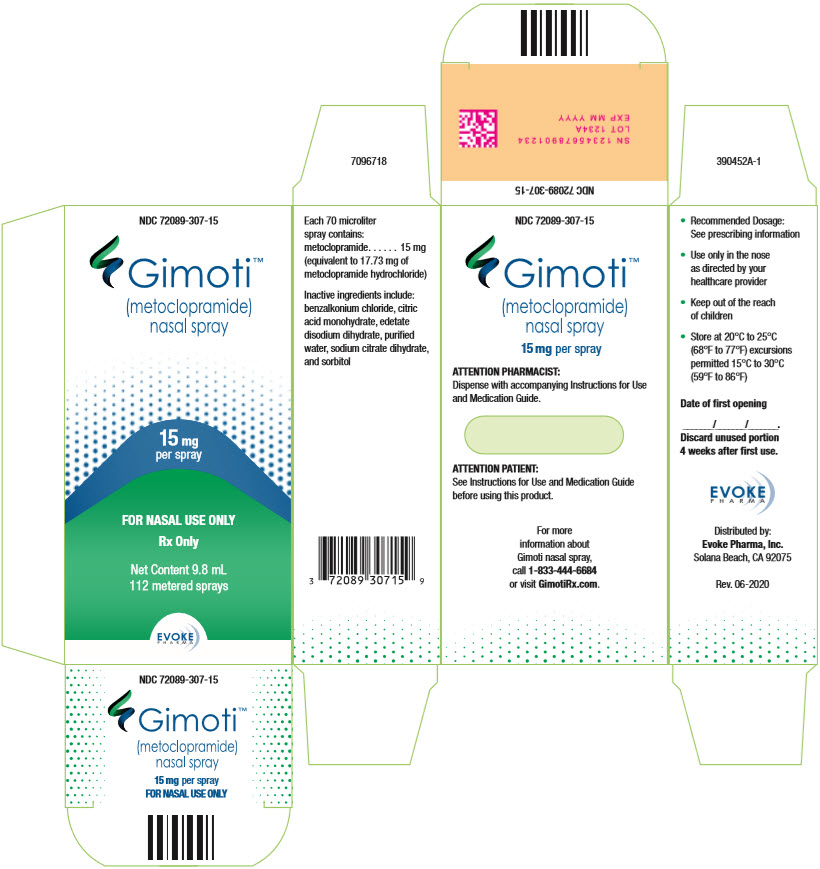 DRUG LABEL: GIMOTI
NDC: 72089-307 | Form: SPRAY
Manufacturer: Evoke Pharma, Inc.
Category: prescription | Type: HUMAN PRESCRIPTION DRUG LABEL
Date: 20260220

ACTIVE INGREDIENTS: METOCLOPRAMIDE HYDROCHLORIDE 15 mg/0.07 mL
INACTIVE INGREDIENTS: BENZALKONIUM CHLORIDE; SORBITOL; EDETATE DISODIUM; CITRIC ACID MONOHYDRATE; TRISODIUM CITRATE DIHYDRATE

HIGHLIGHTS OF PRESCRIBING INFORMATION

These highlights do not include all the information needed to use GIMOTI safely and effectively. See full prescribing information for GIMOTI.
GIMOTI®(metoclopramide) nasal spray
Initial U.S. Approval: 1979

WARNING: TARDIVE DYSKINESIA

See full prescribing information for complete boxed warning.

- Metoclopramide, including GIMOTI, can cause tardive dyskinesia (TD), a potentially irreversible serious movement disorder. In patients treated with metoclopramide, including GIMOTI, the risk of developing TD increases with duration of treatment and total cumulative dosage. (5.1)
- GIMOTI is contraindicated in patients with a history of TD. (4)
- Use GIMOTI for the shortest duration of treatment and periodically reassess the need for continued treatment. (2.2, 5.1)
- Immediately discontinue GIMOTI in patients who develop signs or symptoms of TD. (5.1)
- Avoid a total duration of treatment with metoclopramide products, including GIMOTI, for longer than 12 weeks. If longer-term use is unavoidable, routinely monitor for signs and symptoms of TD. (5.1)

RECENT MAJOR CHANGES

Boxed Warning 2/2026
Dosage and Administration, Recommended Dosage (2.2) 2/2026
Warnings and Precautions, Tardive Dyskinesia (5.1) 2/2026
Warnings and Precautions Other Extrapyramidal Symptoms (5.2) 2/2026

1 INDICATIONS AND USAGE

GIMOTI is a dopamine-2 (D2) antagonist indicated for the relief of symptoms in adults with acute and recurrent diabetic gastroparesis. (1)

Limitations of Use:

GIMOTI is not recommended for use in:

- pediatric patients due to the risk of tardive dyskinesia (TD) and other extrapyramidal symptoms as well as the risk of methemoglobinemia in neonates. (1, 8.4)
- moderate or severe hepatic impairment (Child-Pugh B or C), moderate or severe renal impairment (creatinine clearance less than 60 mL/minute), and patients concurrently using strong CYP2D6 inhibitors due to the risk of increased drug exposure and adverse reactions. (1, 5.9, 7.1)

2 DOSAGE AND ADMINISTRATION

Administration

- See the full prescribing information for complete information on administration. (2.1)

Recommended Dosage

- Adults less than 65 years of age:The recommended dosage is 1 spray (15 mg) in one nostril, 30 minutes before each meal and at bedtime (maximum of 4 sprays daily). (2.2)
- Adults 65 years of age and older:GIMOTI is not recommended in geriatric patients as initial therapy. Geriatric patients receiving an alternative metoclopramide product at a stable dosage of 10 mg four times daily can be switched to GIMOTI 1 spray (15 mg) in one nostril, 30 minutes before each meal and at bedtime (maximum four times daily). (2.2, 8.5)

3 DOSAGE FORMS AND STRENGTHS

Nasal Spray: 15 mg metoclopramide in each 70 microliter spray. (3)

4 CONTRAINDICATIONS

- History of TD or dystonic reaction to metoclopramide (4)
- When stimulation of gastrointestinal motility might be dangerous (4)
- Pheochromocytoma, catecholamine-releasing paragangliomas (4)
- Epilepsy (4)
- Hypersensitivity to metoclopramide (4)

5 WARNINGS AND PRECAUTIONS

- Tardive dyskinesia (TD), other extrapyramidal symptoms (EPS), and neuroleptic malignant syndrome (NMS): Avoid concomitant use of other drugs known to cause TD/EPS/NMS and avoid use in patients with Parkinson's disease. If symptoms occur, discontinue GIMOTI and seek immediate medical attention. (5.1, 5.2, 5.3, 7.1, 7.2)
- Depression and suicidal ideation/suicide: Avoid use. (5.4)

6 ADVERSE REACTIONS

Most common adverse reactions (≥5%) are: dysgeusia, headache, and fatigue. (6)

To report SUSPECTED ADVERSE REACTIONS, contact Evoke Pharma, Inc. at 1-833-4-GIMOTI (1-833-444-6684), or FDA at 1-800-FDA-1088 or www.fda.gov/medwatch.

7 DRUG INTERACTIONS

- Antipsychotics: Potential for additive effects, including TD, EPS, and NMS; avoid concomitant use. (7.1)
- Central nervous system (CNS) depressants: Increased risk of CNS depression. Avoid concomitant use and monitor for adverse reactions. (7.1)
- Monoamine oxidase (MAO) inhibitors: Increased risk of hypertension; avoid concomitant use. (5.5, 7.1)
- Additional drug interactions: See Full Prescribing Information. (7.1, 7.2)

FULL PRESCRIBING INFORMATION

WARNING: TARDIVE DYSKINESIA

- Metoclopramide, including GIMOTI, can cause tardive dyskinesia (TD), a potentially irreversible serious movement disorder. In patients treated with metoclopramide, including GIMOTI, the risk of developing TD increases with duration of treatment and total cumulative dosage [see Warnings and Precautions (5.1)] .
- GIMOTI is contraindicated in patients with a history of TD.
- Use GIMOTI for the shortest duration of treatment and periodically reassess the need for continued treatment.
- Immediately discontinue GIMOTI in patients who develop signs or symptoms of TD [see Warnings and Precautions (5.1)] .
- Avoid a total duration of treatment with metoclopramide products, including GIMOTI, for longer than 12 weeks. If longer-term use is unavoidable, routinely monitor for signs and symptoms of TD [see Warnings and Precautions (5.1)] .

1 INDICATIONS AND USAGE

GIMOTI is indicated for the relief of symptoms in adults with acute and recurrent diabetic gastroparesis.

INDICATIONS AND USAGE

Limitations of Use:

GIMOTI is not recommended for use in:

- pediatric patients due to the risk of developing tardive dyskinesia (TD) and other extrapyramidal symptoms as well as the risk of methemoglobinemia in neonates [see Use in Specific Populations (8.4)].
- moderate or severe hepatic impairment (Child-Pugh B or C), moderate or severe renal impairment (creatinine clearance less than 60 mL/minute), and patients concurrently using strong CYP2D6 inhibitors due to the risk of increased drug exposure and adverse reactions [see Warnings and Precautions (5.9)].

2 DOSAGE AND ADMINISTRATION

2.1 Important Administration and Storage Instructions

- One spray in one nostril administers the appropriate dose.
- Before administering the first dose from a bottle, prime the pump by pressing down on the finger flange and releasing 10 sprays in the air.
- Place the spray nozzle tip under one nostril and lean the head slightly forward so the tip of spray nozzle is aimed away from the septum and toward the back of the nose.
- Close the other nostril with the other index finger. Move spray pump upwards so the tip of the nozzle is in the nostril.
- To ensure a full dose, hold the bottle upright while pressing down firmly and completely on finger flange and release while inhaling slowly through the open nostril.
- Remove spray pump nozzle tip from nostril and exhale slowly through the mouth.
- Wipe the spray nozzle with a clean tissue.

DOSAGE AND ADMINISTRATION

Missed or Incomplete Doses

- If uncertain that the spray entered the nose, do not repeat the dose. Take the next dose at the scheduled time.
- If a dose is missed, take the next dose of GIMOTI at the regularly scheduled time. Do not make up for the missed dose or double the next dose.

DOSAGE AND ADMINISTRATION

Storage

Discard GIMOTI 4 weeks after opening even if the bottle contains unused drug.

2.2 Recommended Dosage

Adults Less Than 65 Years of Age

The recommended dosage of GIMOTI for the treatment of acute and recurrent diabetic gastroparesis in adults is 1 spray (15 mg) in one nostril, 30 minutes before each meal and at bedtime (maximum of four times daily).

Adults 65 Years of Age and Older

Elderly patients may be more sensitive to the adverse effects of metoclopramide and require a lower starting dosage [see Warnings and Precautions (5.1)] . GIMOTI is not recommended in geriatric patients as initial therapy.
Geriatric patients receiving an alternative metoclopramide product at a stable dosage of 10 mg four times daily can be switched to GIMOTI 1 spray (15 mg) in one nostril, 30 minutes before each meal and at bedtime (maximum four times daily).

Treatment Duration

Use GIMOTI for the shortest duration of treatment and periodically reassess the need for continued treatment.
Avoid treatment with metoclopramide, including GIMOTI, for longer than 12 weeks. If longer-term use is unavoidable, routinely monitor for signs and symptoms of TD [see Warnings and Precautions (5.1)] .

3 DOSAGE FORMS AND STRENGTHS

Nasal Spray: 15 mg of metoclopramide in each 70 microliter spray. GIMOTI is an aqueous solution supplied in an amber glass bottle fitted with a metered spray pump attachment.

4 CONTRAINDICATIONS

GIMOTI is contraindicated:

- In patients with a history of tardive dyskinesia (TD) or a dystonic reaction to metoclopramide [see Warnings and Precautions (5.1, 5.2)] .
- When stimulation of gastrointestinal motility might be dangerous (e.g., in the presence of gastrointestinal hemorrhage, mechanical obstruction, or perforation).
- In patients with pheochromocytoma or other catecholamine-releasing paragangliomas. Metoclopramide may cause a hypertensive/pheochromocytoma crisis, probably due to release of catecholamines from the tumor [see Warnings and Precautions (5.5)] .
- In patients with epilepsy. Metoclopramide may increase the frequency and severity of seizures [see Adverse Reactions (6)] .
- In patients with hypersensitivity to metoclopramide. Reactions have included laryngeal and glossal angioedema and bronchospasm [see Adverse Reactions (6)] .

5 WARNINGS AND PRECAUTIONS

5.1 Tardive Dyskinesia

Metoclopramide, including GIMOTI, can cause tardive dyskinesia (TD), a syndrome of potentially irreversible and disfiguring involuntary movements of the face or tongue, and sometimes of the trunk and/or extremities. Metoclopramide, including GIMOTI, may also suppress, or partially suppress, the signs of TD, and may delay the diagnosis of TD because it may mask the underlying disease process. The effect of this symptomatic suppression upon the long-term course of TD is unknown. TD may remit, partially or completely, if GIMOTI treatment is discontinued.

In patients treated with metoclopramide, including GIMOTI, the risk of developing TD and the likelihood that TD will become irreversible increases with duration of treatment and total cumulative dosage. Additionally, the risk of developing TD is increased in elderly patients, especially in elderly women [see Use in Specific Populations (8.5)] , and in patients with diabetes mellitus.

Prevention, Mitigation, and Monitoring for TD

- GIMOTI is contraindicated in patients with a history of TD.
- Avoid use of GIMOTI in patients receiving concomitant antipsychotics due to the potential additive effects of TD [see Drug Interactions (7.1)] .
- GIMOTI is not recommended in geriatric patients as initial therapy [see Dosage and Administration (2.2)] .
- Use GIMOTI for the shortest duration of treatment and periodically reassess the need for continued treatment.
- Immediately discontinue GIMOTI immediately in patients who develop signs and symptoms of TD.
- Avoid a total duration of treatment with metoclopramide products, including GIMOTI, for longer than 12 weeks. If longer-term use is unavoidable, routinely monitor for signs and symptoms of TD.
- If patients have continued TD symptoms, consider TD treatment.

5.2 Other Extrapyramidal Symptoms

In addition to TD, metoclopramide may cause other extrapyramidal symptoms (EPS), parkinsonian symptoms, and motor restlessness. Advise patients to seek immediate medical attention if such symptoms occur and to discontinue GIMOTI.

- Extrapyramidal symptoms (EPS), such as acute dystonic reactions, occurred in patients treated with oral metoclopramide dosages of 30 mg to 40 mg daily. Such reactions occurred more frequently in adults less than 30 years of age and at higher than recommended dosages. EPS occurred more frequently in pediatric patients compared to adults (GIMOTI is not approved for use in pediatric patients). Symptoms can occur in the first 24 to 48 hours after starting metoclopramide. Symptoms included involuntary movements of limbs and facial grimacing, torticollis, oculogyric crisis, rhythmic protrusion of tongue, bulbar type of speech, trismus, or dystonic reactions resembling tetanus. Rarely, dystonic reactions were present as stridor and dyspnea, possibly due to laryngospasm. Diphenhydramine hydrochloride or benztropine mesylate may be used to treat these adverse reactions. Avoid GIMOTI in patients receiving other drugs that can cause EPS (e.g., antipsychotics).
- Parkinsonian symptoms (bradykinesia, tremor, cogwheel rigidity, mask-like facies) have occurred after starting metoclopramide, more commonly within the first 6 months, but also after longer periods. Symptoms generally have subsided within 2 to 3 months after discontinuation of metoclopramide. Avoid GIMOTI in patients with Parkinson’s disease and other patients being treated with antiparkinsonian drugs due to potential exacerbation of symptoms. If treatment is unavoidable, use GIMOTI for the shortest duration of treatment and periodically reassess the need for continued treatment. Routinely monitor for signs and symptoms of Parkinson’s disease [see Dosage and Administration (2.2)] .
- Motor restlessness (akathisia) has developed and consisted of feelings of anxiety, agitation, jitteriness, and insomnia, as well as inability to sit still, pacing, and foot tapping. Discontinue GIMOTI if these symptoms develop.

5.3 Neuroleptic Malignant Syndrome

Metoclopramide may cause a potentially fatal symptom complex called neuroleptic malignant syndrome (NMS). NMS has been reported in association with metoclopramide overdosage and concomitant treatment with another drug associated with NMS. Avoid GIMOTI in patients receiving other drugs associated with NMS, including typical and atypical antipsychotics.

Clinical manifestations of NMS include hyperpyrexia, muscle rigidity, altered mental status, and manifestations of autonomic instability (irregular pulse or blood pressure, tachycardia, diaphoresis, and cardiac arrhythmias). Additional signs may include elevated creatine phosphokinase, myoglobinuria (rhabdomyolysis), and acute renal failure. Patients with such symptoms should be evaluated immediately.

In the diagnostic evaluation, consider the presence of other serious medical conditions (e.g., pneumonia, systemic infection) and untreated or inadequately treated extrapyramidal signs and symptoms. Other important considerations in the differential diagnosis include central anticholinergic toxicity, heat stroke, malignant hyperthermia, drug fever, serotonin syndrome, and primary central nervous system pathology.

Management of NMS includes:

- Immediate discontinuation of GIMOTI and other drugs not essential to concurrent therapy [see Drug Interactions (7.1)] .
- Intensive symptomatic treatment and medical monitoring.
- Treatment of any concomitant serious medical problems for which specific treatments are available.

5.4 Depression

Depression has occurred in metoclopramide-treated patients with and without a history of depression. Symptoms have included suicidal ideation and suicide. Avoid GIMOTI use in patients with a history of depression.

5.5 Hypertension

Metoclopramide may elevate blood pressure. In one study in hypertensive patients, intravenously administered metoclopramide was shown to release catecholamines; hence, avoid GIMOTI use in patients with hypertension or in patients taking monoamine oxidase inhibitors [see Drug Interactions (7.1)] .

There are also clinical reports of hypertensive crises in patients with undiagnosed pheochromocytoma. GIMOTI is contraindicated in patients with pheochromocytoma or other catecholamine-releasing paragangliomas [see Contraindications (4)]. Discontinue GIMOTI in any patient with a rapid rise in blood pressure.

5.6 Fluid Retention

Because metoclopramide produces a transient increase in plasma aldosterone, patients with cirrhosis or congestive heart failure may be at risk of developing fluid retention and volume overload. Discontinue GIMOTI if any of these adverse reactions occur.

5.7 Hyperprolactinemia

As with other dopamine D2receptor antagonists, metoclopramide elevates prolactin levels. Hyperprolactinemia may suppress hypothalamic gonadotropin-releasing hormone, resulting in reduced pituitary gonadotropin secretion. This, in turn, may inhibit reproductive function by impairing gonadal steroidogenesis in both female and male patients. Galactorrhea, amenorrhea, gynecomastia, and impotence have been reported with prolactin-elevating drugs, including metoclopramide.

Hyperprolactinemia may potentially stimulate prolactin-dependent breast cancer. However, some clinical studies and epidemiology studies have not shown an association between administration of dopamine D2receptor antagonists and tumorigenesis in humans [see Nonclinical Toxicology (13.1)].

5.8 Effects on the Ability to Drive and Operate Machinery

Metoclopramide may impair the mental and/or physical abilities required for the performance of hazardous tasks such as operating machinery or driving a motor vehicle. Concomitant use of central nervous system (CNS) depressants or drugs associated with EPS may increase this effect (e.g., alcohol, sedatives, hypnotics, opiates, and anxiolytics). Avoid GIMOTI or the interacting drug, depending on the importance of the drug to the patient [see Drug Interactions (7.1)].

5.9 Risk of Adverse Reactions with GIMOTI in Patients with Moderate or Severe Renal and Hepatic Impairment, CYP2D6 Poor Metabolizers and Patients Taking Strong CYP2D6 Inhibitors

Patients with moderate or severe renal or hepatic impairment, patients who are CYP2D6 poor metabolizers, and patients concurrently using strong CYP2D6 inhibitors have increased exposure to metoclopramide from GIMOTI due to reduced metabolism or excretion which may lead to an increased risk of adverse reactions, including tardive dyskinesia. Use of GIMOTI is not recommended in these patient populations since the dose of GIMOTI cannot be adjusted to reduce exposure [see Drug Interactions (7.1), Use in Specific Populations (8.6, 8.7, 8.9)] .

6 ADVERSE REACTIONS

The following adverse reactions are described, or described in greater detail, in other sections of the labeling:

- Tardive dyskinesia [see Boxed Warning and Warnings and Precautions (5.1)]
- Other extrapyramidal symptoms [see Warnings and Precautions (5.2)]
- Neuroleptic malignant syndrome [see Warnings and Precautions (5.3)]
- Depression [see Warnings and Precautions (5.4)]
- Hypertension [see Warnings and Precautions (5.5)]
- Fluid retention [see Warnings and Precautions (5.6)]
- Hyperprolactinemia [see Warnings and Precautions (5.7)]
- Effects on the ability to drive and operate machinery [see Warnings and Precautions (5.8)]

The following adverse reactions have been identified from clinical studies or postmarketing reports of metoclopramide. Because these reactions are reported voluntarily from a population of uncertain size, it is not always possible to reliably estimate their frequency or establish a causal relationship to drug exposure.

The safety of GIMOTI was evaluated in clinical trials of patients with gastroparesis and established in clinical trials of oral metoclopramide.

Safety of GIMOTI

In a randomized, placebo-controlled clinical trial of 190 male and female patients of GIMOTI 14 mg, a slightly lower than recommended dosage, administered nasally four times daily for 4 weeks, dysgeusia was the most commonly reported adverse reaction (15% of GIMOTI-treated patients and 4% of placebo-treated patients). Other adverse reactions were similar to those reported for oral metoclopramide.

Safety of Oral Metoclopramide

The most common adverse reactions (in approximately 10% of patients receiving the recommended oral metoclopramide dosage of 10 mg four times daily) were restlessness, drowsiness, fatigue, and lassitude. In general, the incidence of adverse reactions correlated with the dosage and duration of metoclopramide administration.

Adverse reactions, especially those involving the nervous system, occurred after stopping metoclopramide including dizziness, nervousness, and headaches.

Central Nervous System Disorders

- Tardive dyskinesia, acute dystonic reactions, drug-induced parkinsonism, akathisia, and other extrapyramidal symptoms
- Convulsive seizures
- Hallucinations
- Restlessness, drowsiness, fatigue, and lassitude occurred in approximately 10% of patients who received metoclopramide orally 10 mg four times daily. Insomnia, headache, confusion, dizziness, or depression with suicidal ideation occurred less frequently.
- Neuroleptic malignant syndrome, serotonin syndrome (in combination with serotonergic agents)

Endocrine Disorders: Fluid retention secondary to transient elevation of aldosterone, galactorrhea, amenorrhea, gynecomastia, impotence secondary to hyperprolactinemia

Cardiovascular Disorders: Acute congestive heart failure, possible atrioventricular block, hypotension, hypertension, supraventricular tachycardia, bradycardia, fluid retention

Gastrointestinal Disorders: Nausea, bowel disturbances (primarily diarrhea)

Hepatic Disorders: Hepatotoxicity, characterized by, e.g., jaundice and altered liver function tests, when metoclopramide was administered with other drugs with known hepatotoxic potential

Renal and Urinary Disorders: Urinary frequency, urinary incontinence

Hematologic Disorders: Agranulocytosis, neutropenia, leukopenia, methemoglobinemia, sulfhemoglobinemia

Hypersensitivity Reactions: Bronchospasm (especially in patients with a history of asthma), urticaria, rash, angioedema, including glossal or laryngeal edema

Eye Disorders: Visual disturbances

Metabolism Disorders: Porphyria

7 DRUG INTERACTIONS

7.1 Effects of Other Drugs on Metoclopramide

Table 1 displays the effects of other drugs on metoclopramide.

Table 1. Effects of Other Drugs on Metoclopramide
Antipsychotics
Clinical Impact | Potential for additive effects, including increased frequency and severity of tardive dyskinesia (TD), other extrapyramidal symptoms (EPS), and neuroleptic malignant syndrome (NMS).
Intervention | Avoid concomitant use [see Warnings and Precautions (5.1, 5.2, 5.3)].
Strong CYP2D6 Inhibitors, not Included in Antipsychotic Category Above
Clinical Impact | Increased plasma concentrations of metoclopramide; risk of exacerbation of extrapyramidal symptoms [see Clinical Pharmacology (12.3)].
Intervention | Use of GIMOTI is not recommended [see Warnings and Precautions (5.9)] .
Examples | quinidine, bupropion, fluoxetine, and paroxetine
Monoamine Oxidase Inhibitors
Clinical Impact | Increased risk of hypertension [see Warnings and Precautions (5.5)].
Intervention | Avoid concomitant use.
Central Nervous System (CNS) Depressants
Clinical Impact | Increased risk of CNS depression [see Warnings and Precautions (5.8)].
Intervention | Avoid GIMOTI or the interacting drug, depending on the importance of the drug to the patient.
Examples | alcohol, sedatives, hypnotics, opiates, and anxiolytics
Drugs that Impair Gastrointestinal Motility
Clinical Impact | Potential for decreased effect of metoclopramide due to opposing effects on gastrointestinal motility.
Intervention | Monitor for reduced effect on gastrointestinal motility.
Examples | antiperistaltic antidiarrheal drugs, anticholinergic drugs, and opiates
Dopaminergic Agonists and Other Drugs that Increase Dopamine Concentrations
Clinical Impact | Decreased therapeutic effect of metoclopramide due to opposing effects on dopamine.
Intervention | Monitor for reduced therapeutic effect.
Examples | apomorphine, bromocriptine, cabergoline, levodopa, pramipexole, ropinirole, and rotigotine

7.2 Effects of Metoclopramide on Other Drugs

Table 2 displays the effects of metoclopramide on other drugs.

Table 2. Effects of Metoclopramide on Other Drugs
Dopaminergic Agonists and Drugs Increasing Dopamine Concentrations
Clinical Impact | Opposing effects of metoclopramide and the interacting drug on dopamine. Potential exacerbation of symptoms (e.g., parkinsonian symptoms).
Intervention | Avoid concomitant use [see Warnings and Precautions (5.2)] .
Examples | Apomorphine, bromocriptine, cabergoline, levodopa, pramipexole, ropinirole, rotigotine
Succinylcholine, Mivacurium
Clinical Impact | Metoclopramide inhibits plasma cholinesterase leading to enhanced neuromuscular blockade.
Intervention | Monitor for signs and symptoms of prolonged neuromuscular blockade
Drugs with Absorption Altered due to Increased Gastrointestinal Motility
Clinical Impact | The effect of metoclopramide on other drugs is variable. Increased gastrointestinal (GI) motility by metoclopramide may impact absorption of other drugs leading to decreased or increased drug exposure.
Intervention | Drugs with Decreased Absorption (e.g., digoxin, atovaquone, posaconazole oral suspension [Interaction does not apply to posaconazole delayed-release tablet.] , fosfomycin) : Monitor for reduced therapeutic effect of the interacting drug. For digoxin, monitor therapeutic drug concentrations and increase the digoxin dose as needed (see prescribing information for digoxin). Drugs with Increased Absorption (e.g., sirolimus, tacrolimus, cyclosporine): Monitor therapeutic drug concentrations and adjust the dose as needed. See prescribing information for the interacting drug.
Insulin
Clinical Impact | Increased GI motility by metoclopramide may increase delivery of food to the intestines and increase blood glucose.
Intervention | Monitor blood glucose and adjust insulin dosage regimen as needed.

8 USE IN SPECIFIC POPULATIONS

8.1 Pregnancy

Risk Summary

Published studies, including retrospective cohort studies, national registry studies, and meta-analyses, do not report a consistent pattern or a consistently increased risk of adverse pregnancy-related outcomes with oral use of metoclopramide during pregnancy. However, available data from a case report of GIMOTI use in pregnancy is insufficient to evaluate for a drug-associated risk of major birth defects, miscarriage, or adverse maternal or fetal outcomes.

There are potential risks to the neonate following exposure in uteroto metoclopramide during delivery (see Clinical Considerations).

In animal reproduction studies, no adverse developmental effects were observed with oral administration of metoclopramide to pregnant rats and rabbits at exposures about 6 and 12 times the maximum recommended human dose (MRHD) (see Data) .

The background risk of major birth defects and miscarriage for the indicated population is unknown. All pregnancies have a background risk of birth defects, loss, or other adverse outcomes. In the U.S. general population, the estimated background risk of major birth defects and miscarriage in clinically recognized pregnancies is 2% to 4% and 15% to 20%, respectively.

Clinical Considerations

Fetal/Neonatal Adverse Reactions

Metoclopramide crosses the placental barrier and may cause extrapyramidal signs and methemoglobinemia in neonates with maternal administration during delivery. Monitor neonates for extrapyramidal signs [see Warnings and Precautions (5.1, 5.2), Use in Specific Populations (8.4)] .

Data

Animal Data

Reproduction studies have been performed following administration of oral metoclopramide during organogenesis in pregnant rats at about 6 times the MRHD calculated on body surface area and in pregnant rabbits at about 12 times the MRHD calculated on body surface area. No evidence of adverse developmental effects due to metoclopramide was observed.

8.2 Lactation

Risk Summary

There are no data on the presence of metoclopramide in human milk following nasal administration; however, published data report the presence of metoclopramide in human milk in variable amounts following oral administration (see Data) . Systemic exposure following nasal administration of GIMOTI 15 mg is expected to be similar to oral administration of metoclopramide 10 mg [see Clinical Pharmacology (12.3)] . Breastfed infants exposed to metoclopramide have experienced gastrointestinal adverse reactions, including intestinal discomfort and increased intestinal gas formation (see Clinical Considerations) . Metoclopramide elevates prolactin levels [see Warnings and Precautions (5.7)] ; however, the published data are not adequate to support drug effects on milk production. The developmental and health benefits of breastfeeding should be considered along with the mother's clinical need for GIMOTI and any potential adverse effects on the breastfed child from GIMOTI or from the underlying maternal condition.

Clinical Considerations

Monitor breastfeeding neonates because metoclopramide may cause extrapyramidal signs (dystonias) and methemoglobinemia [see Warnings and Precautions (5.1, 5.2), Use in Specific Populations (8.4)] .

Data

In published clinical studies, the estimated amount of metoclopramide received by the breastfed infant was less than 10% of the maternal weight-adjusted oral dose. In one study, the estimated daily amount of metoclopramide received by infants from breast milk ranged from 6 to 24 mcg/kg/day in early puerperium (3 to 9 days postpartum) and from 1 to 13 mcg/kg/day at 8 to 12 weeks postpartum.

8.4 Pediatric Use

Metoclopramide is not recommended for use in pediatric patients due to the risk of tardive dyskinesia (TD) and other extrapyramidal symptoms as well as the risk of methemoglobinemia in neonates. The safety and effectiveness of GIMOTI in pediatric patients have not been established.

Dystonias and other extrapyramidal symptoms associated with metoclopramide are more common in pediatric patients than in adults [see Indications and Usage (1), Warnings and Precautions (5.1, 5.2)] . In addition, neonates have reduced levels of NADH-cytochrome b5reductase, making them more susceptible to methemoglobinemia, a possible adverse reaction of metoclopramide use in neonates [see Use in Specific Populations (8.8)] .

8.5 Geriatric Use

Metoclopramide is known to be substantially excreted by the kidney, and the risk of adverse reactions, including tardive dyskinesia (TD), may be greater in patients with impaired renal function [see Warnings and Precautions (5.1), Use in Specific Populations (8.6), Clinical Pharmacology (12.3)] . Elderly patients are more likely to have decreased renal function and may be more sensitive to the adverse effects of metoclopramide, especially elderly women, and require a lower starting dosage. GIMOTI is not recommended in geriatric patients as initial therapy. Geriatric patients receiving an alternative metoclopramide product at a stable dosage of 10 mg four times daily can be switched to GIMOTI [see Dosage and Administration (2.2)].

8.6 Renal Impairment

The clearance of metoclopramide is decreased and the systemic exposure is increased in patients with moderate to severe renal impairment compared to patients with normal renal function, which may increase the risk of adverse reactions [see Clinical Pharmacology (12.3)] . GIMOTI is not recommended in patients with moderate and severe renal impairment (creatinine clearance less than 60 mL/minute), including those receiving hemodialysis and continuous ambulatory peritoneal dialysis [see Warnings and Precautions (5.9)] . Use the recommended dosage of GIMOTI in patients with mild renal impairment (creatinine clearance 60 mL/minute or greater) [see Dosage and Administration (2.2)].

8.7 Hepatic Impairment

Patients with severe hepatic impairment (Child-Pugh C) have reduced systemic metoclopramide clearance (by approximately 50%) compared to patients with normal hepatic function [see Clinical Pharmacology (12.3)] . The resulting increase in metoclopramide blood concentrations increases the risk of adverse reactions. There are no pharmacokinetic data in patients with moderate hepatic impairment (Child-Pugh B). GIMOTI is not recommended in patients with moderate or severe (Child-Pugh B or C) hepatic impairment [see Warnings and Precautions (5.9)]. Use the recommended dosage of GIMOTI in patients with mild hepatic impairment (Child-Pugh A) [see Dosage and Administration (2.2)] .

Metoclopramide, by producing a transient increase in plasma aldosterone, may increase the risk of fluid retention in patients with hepatic impairment [see Warnings and Precautions (5.6)] . Monitor patients with hepatic impairment for the occurrence of fluid retention and volume overload.

8.8 NADH-Cytochrome b5Reductase Deficiency

Metoclopramide-treated patients with NADH-cytochrome b5reductase deficiency are at an increased risk of developing methemoglobinemia and/or sulfhemoglobinemia. For patients with glucose-6-phosphate dehydrogenase (G6PD) deficiency with metoclopramide-induced methemoglobinemia, methylene blue treatment is not recommended. Methylene blue may cause hemolytic anemia in patients with G6PD deficiency, which may be fatal [see Overdosage (10)].

8.9 CYP2D6 Poor Metabolizers

Metoclopramide is a substrate of CYP2D6. The elimination of metoclopramide may be slowed in patients who are CYP2D6 poor metabolizers (compared to patients who are CYP2D6 intermediate, extensive, or ultra-rapid metabolizers), possibly increasing the risk of dystonic and other adverse reactions to metoclopramide [see Clinical Pharmacology (12.3)]. GIMOTI is not recommended in patients who are CYP2D6 poor metabolizers [see Warnings and Precautions (5.9)].

10 OVERDOSAGE

Manifestations of metoclopramide overdosage included drowsiness, disorientation, extrapyramidal reactions, other adverse reactions associated with metoclopramide use (including, e.g., methemoglobinemia), and sometimes death. Neuroleptic malignant syndrome (NMS) has been reported in association with metoclopramide overdose and concomitant treatment with another drug associated with NMS [see Warnings and Precautions (5.1, 5.2, 5.3)].

There are no specific antidotes for metoclopramide overdosage. If over-exposure occurs, call your Poison Control Center at 1-800-222-1222 for current information on the management of poisoning or overdosage .

Methemoglobinemia can be reversed by the intravenous administration of methylene blue. However, methylene blue may cause hemolytic anemia in patients with G6PD deficiency, which may be fatal.

Hemodialysis and continuous ambulatory peritoneal dialysis do not remove significant amounts of metoclopramide.

11 DESCRIPTION

Metoclopramide hydrochloride, the active ingredient in GIMOTI, is a dopamine-2 receptor antagonist. Metoclopramide hydrochloride is a white, crystalline, odorless substance, freely soluble in water. Its chemical name is 4-amino-5-chloro-N-[2-(diethylamino)ethyl]-2-methoxy benzamide monohydrochloride monohydrate.

The molecular formula is C14H22ClN3O2∙HCl∙H2O. Its molecular weight is 354.3. The structural formula is:

GIMOTI (metoclopramide) nasal spray is for nasal administration. The product is supplied as an aqueous solution with a pH of 5.5 ± 0.5 in a 10 mL amber glass vial fitted with a metered spray pump attachment. Each unit contains 9.8 mL.

Each 70 microliter spray contains 15 mg metoclopramide, equivalent to 17.73 mg of metoclopramide hydrochloride. Inactive ingredients consist of benzalkonium chloride, citric acid monohydrate, edetate disodium dihydrate, purified water, sodium citrate dihydrate, and sorbitol.

12 CLINICAL PHARMACOLOGY

12.1 Mechanism of Action

Metoclopramide stimulates motility of the upper gastrointestinal tract without stimulating gastric, biliary, or pancreatic secretions. The exact mechanism of action of metoclopramide in the treatment of gastroesophageal reflux and acute and recurrent diabetic gastroparesis has not been fully established. It seems to sensitize tissues to the action of acetylcholine. The effect of metoclopramide on motility is not dependent on intact vagal innervation, but it can be abolished by anticholinergic drugs.

Metoclopramide increases the tone and amplitude of gastric (especially antral) contractions, relaxes the pyloric sphincter and the duodenal bulb, and increases peristalsis of the duodenum and jejunum resulting in accelerated gastric emptying and intestinal transit. It increases the resting tone of the lower esophageal sphincter. It has little, if any, effect on the motility of the colon or gallbladder.

12.2 Pharmacodynamics

Cardiac Electrophysiology

In a randomized, double-blind, positive-controlled thorough ECG study in 48 healthy subjects, a single administration of 80 mg metoclopramide nasal spray (approximately 5 times the recommended GIMOTI dose) had no effect on the QTc interval.

12.3 Pharmacokinetics

Absorption

The absolute bioavailability of metoclopramide following nasal administration of 10 mg metoclopramide is 47% in healthy subjects compared to intravenous injection of metoclopramide 10 mg. The systemic absorption after nasal administration is lower than that after oral administration given the same dose. Following nasal administration of GIMOTI 15 mg in healthy subjects, the systemic exposure (Cmaxand AUC) to metoclopramide and the time to reach Cmax (Tmax) were similar to orally administered 10 mg metoclopramide tablet.

After single nasal administration of metoclopramide at doses ranging from 10 mg to 80 mg in healthy subjects, there was a dose-proportional increase in the mean values for Cmax and AUC.

The pharmacokinetic parameters of metoclopramide in healthy subjects following a single nasal administration of GIMOTI 15 mg are summarized in Table 3.

Table 3. Summary of Metoclopramide Pharmacokinetic Parameters in Healthy Subjects after a Single Nasal Administration of GIMOTI 15 mg
Parameter [Arithmetic mean (SD) except t max for which the median (range) is reported.] | GIMOTI 15 mg
N | 94
Cmax(ng/mL) | 41.0 (19.9)
tmax(h) | 1.25 (0.50 – 3.50)
AUC0-t(ng∙h/mL) | 349 (174.7)
AUC0-inf(ng∙h/mL) [N = 93] | 367 (184.8)
t1/2(h) | 8.1 (2.0)

Distribution

Metoclopramide is not extensively bound to plasma proteins (about 30%). The whole body volume of distribution is high (about 3.5 L/kg), which suggests extensive distribution of drug to the tissues.

Elimination

The mean elimination half-life in individuals with normal renal function is approximately 8 hours for administration with GIMOTI 15 mg.

Metabolism:Metoclopramide undergoes enzymatic metabolism via oxidation as well as glucuronide and sulfate conjugation reactions in the liver. Monodeethylmetoclopramide, a major oxidative metabolite, is formed primarily by CYP2D6, an enzyme subject to genetic variability [see Warnings and Precautions (5.9), Use in Specific Populations (8.9)] .

Excretion:Approximately 85% of the radioactivity of an orally administered dose appeared in the urine within 72 hours. After oral administration of 10 or 20 mg, a mean of 18% and 22% of the dose, respectively, was recovered as free metoclopramide in urine within 36 hours.

Specific Populations

Patients with Renal Impairment:In a study of 24 patients with varying degrees of renal impairment (moderate, severe, and end-stage renal disease [ESRD] requiring dialysis), the systemic exposure (AUC) of metoclopramide following oral administration in patients with moderate to severe renal impairment was about 2-fold the AUC in subjects with normal renal function. The AUC of metoclopramide in patients with ESRD on dialysis was about 3.5-fold the AUC in subjects with normal renal function [see Warnings and Precautions (5.9), Use in Specific Populations (8.6)].

Patients with Hepatic Impairment:In a group of 8 patients with severe hepatic impairment (Child-Pugh C), the average metoclopramide clearance was reduced by approximately 50% compared to patients with normal hepatic function after administration of oral metoclopramide [see Warnings and Precautions (5.9), Use in Specific Populations (8.7)].

Sex and Body Weight:The AUC0-tand Cmax of metoclopramide were 34% and 42% higher in females than in males, respectively, following administration of metoclopramide nasal spray to healthy subjects. Based on population pharmacokinetic analysis, lean body weight (34.3 to 93.5 kg) has a significant impact on metoclopramide pharmacokinetics, with lower systemic exposure expected with higher lean body weight. The clinical significance of these findings is unknown.

Drug Interactions

Effect of Metoclopramide on CYP2D6 Substrates

Although in vitrostudies suggest that metoclopramide can inhibit CYP2D6, metoclopramide is unlikely to interact with CYP2D6 substrates in vivoat therapeutically relevant concentrations.

Effect of CYP2D6 Inhibitors on Metoclopramide

Metoclopramide 20 mg was orally administered as a single dose to 24 healthy males, without (Period 1) and with (Period 2) a concomitant dose of fluoxetine 60 mg (a strong CYP2D6 inhibitor). Between the two periods, fluoxetine was administered orally for 8 days. The subjects who received concomitant metoclopramide and fluoxetine had a 40% and 90% increase in metoclopramide Cmaxand AUC0-inf, respectively, compared to subjects who received metoclopramide alone. The mean half-life for metoclopramide was increased from 5.5 (±1.1) hours to 8.5 (±2.2) hours with concomitant fluoxetine [see Warnings and Precautions (5.9), Drug Interactions (7.1)] .

13 NONCLINICAL TOXICOLOGY

13.1 Carcinogenesis, Mutagenesis, Impairment of Fertility

Carcinogenesis

A 77-week study was conducted in rats with oral metoclopramide doses up to 40 mg/kg/day (about 6 times the maximum recommended human dose on body surface area basis). Metoclopramide elevated prolactin levels, and the elevation persisted during chronic administration. An increase in mammary neoplasms was found in rodents after chronic administration of metoclopramide [see Warnings and Precautions (5.7)]. In a rat model for assessing the tumor promotion potential, a 2-week oral treatment with metoclopramide at a dose of 260 mg/kg/day (about 35 times the MRHD based on body surface area) enhanced the tumorigenic effect of N-nitrosodiethylamine.

Mutagenesis

Metoclopramide was positive in the in vitroChinese hamster lung cell/HGPRT forward mutation assay for mutagenic effects and in the in vitrohuman lymphocyte chromosome aberration assay for clastogenic effects. It was negative in the in vitroAmes mutation assay, the in vitrounscheduled DNA synthesis assay with rat and human hepatocytes, and the in vivorat micronucleus assay.

Impairment of Fertility

Metoclopramide at intramuscular doses up to 20 mg/kg/day (about 3 times the maximum recommended human dose based on body surface area) was found to have no effect on fertility and reproductive performance of male and female rats.

14 CLINICAL STUDIES

The effectiveness of GIMOTI has been established based on studies of oral metoclopramide for the relief of symptoms in adults with acute and recurrent diabetic gastroparesis.

16 HOW SUPPLIED/STORAGE AND HANDLING

GIMOTI (metoclopramide) nasal spray is supplied as a solution of metoclopramide in a 10 mL Type 1 amber glass bottle fitted with a metered spray pump attachment, a protective cap, and a safety clip. Each box of GIMOTI (NDC 72089-307-15) contains 1 bottle, with FDA-approved Patient Labeling (see Instructions for Use for proper actuation of the device).

Each actuation delivers 15 mg of metoclopramide. Each bottle contains 9.8 mL which is sufficient for 4 weeks of 4 times a day use.

STORAGE AND HANDLING

Store at 20°C to 25°C (68°F to 77°F) excursions permitted 15°C to 30°C (59°F and 86°F) [ see USP Controlled Room Temperature].

Discard GIMOTI 4 weeks after opening even if the bottle contains unused medicine.

17 PATIENT COUNSELING INFORMATION

Advise the patient or caregiver to read the FDA-approved patient labeling (Medication Guide and Instructions for Use).

Adverse Reactions

Tardive Dyskinesia and/or other Extrapyramidal Reactions

Inform patients that GIMOTI may cause tardive dyskinesia or other extrapyramidal symptoms, parkinsonian symptoms, and motor restlessness. Instruct patients to immediately discontinue GIMOTI and contact their healthcare provider if symptoms occur [see Warnings and Precautions (5.1, 5.2)] .

Neuroleptic Malignant Syndrome

Inform patients that serious neuroleptic malignant syndrome (NMS) has been reported in association with concomitant treatment with another drug associated with NMS. Advise patients to report all prescription and over-the-counter medications to the healthcare provider. Instruct patients to immediately discontinue GIMOTI and seek medical attention if symptoms occur [see Warnings and Precautions (5.3)]

Depression and/or Possible Suicidal Ideation

Inform patients that symptoms of new onset or worsening depression as well as suicidal ideation have been reported in patients taking metoclopramide. Instruct patients to immediately discontinue GIMOTI and contact their healthcare provider if any of these symptoms occur [see Warnings and Precautions (5.4)]

Drug Interactions

Inform the patients or their caregivers that concomitant treatment with numerous other medications can precipitate or worsen serious adverse reactions such as tardive dyskinesia or other extrapyramidal reactions, neuroleptic malignant syndrome, and CNS depression [see Drug Interactions (7.1, 7.2)] . Explain that the prescriber of any other medication must be made aware that the patient is taking GIMOTI.

Effects on the Ability to Drive and Operate Machinery

Inform the patient or their caregiver that GIMOTI may cause drowsiness or dizziness, or otherwise impair the mental and/or physical abilities required for the performance of hazardous tasks such as operating machinery or driving a motor vehicle [see Warnings and Precautions (5.8)] .

Administration Instructions [see Dosage and Administration (2.1)]

Advise the patients or their caregiver to read the Instructions for Use on how to appropriately administer GIMOTI:

- One spray in one nostril administers the appropriate dose.
- Before administering the first dose from a bottle, prime the pump by pressing down on the finger flange and releasing 10 sprays in the air.
- Place the spray nozzle tip under one nostril and lean the head slightly forward so the tip of spray nozzle is aimed away from the septum and toward the back of the nose.
- Close the other nostril with the other index finger. Move spray pump upwards so the tip of the nozzle is in the nostril.
- To ensure a full dose, hold the bottle upright while pressing down firmly and completely on finger flange and release while inhaling slowly through the open nostril.
- Remove spray pump nozzle tip from nostril and exhale slowly through the mouth.
- Wipe the spray nozzle with a clean tissue.

Missed or Incomplete Doses

- If uncertain that the spray entered the nose, do not repeat the dose. Take the next dose at the scheduled time.
- If a dose is missed, take the next dose of GIMOTI at the regularly scheduled time. Do not make up for the missed dose or double the next dose.

Manufactured for: Evoke Pharma, Inc.
Solana Beach, CA 92075 USA
By: Patheon, a Division of Thermo Fisher
Bourgoin Jallieu Cedex, 38307, France

© 2026 Evoke Pharma, Inc. All rights reserved.

Medication Guide
GIMOTI™ (jye-MOH-tee)
(metoclopramide)
nasal spray

Read this Medication Guide before you start taking GIMOTI and each time you get a refill. There may be new information. If you take another product that contains metoclopramide (such as REGLAN tablets, REGLAN injection, metoclopramide orally disintegrating tablets [ODT], or metoclopramide oral solution), you should read the Medication Guide that comes with that product. Some of the information may be different. This information does not take the place of talking with your healthcare provider about your medical condition or your treatment.

What is the most important information I should know about GIMOTI?
GIMOTI can cause serious side effects, including:
Tardive dyskinesia (abnormal muscle movements).

- These movements happen mostly in the face or tongue and sometimes in the arms or legs. You cannot control these movements.
- These symptoms may not go away even after stopping GIMOTI.

Your chances for getting tardive dyskinesia increase:

- the longer you take GIMOTI and the more GIMOTI you take.
  - Use for the shortest time needed.
  - You should not take products containing metoclopramide (including GIMOTI) for more than 12 weeks. If you require treatment for longer than 12 weeks, your healthcare provider should frequently monitor you for signs and symptoms of tardive dyskinesia
- if you are older, especially if you are an older woman.
- because you have diabetes.

It is not possible for your healthcare provider to know if you will get tardive dyskinesia if you take GIMOTI.
Stop taking GIMOTI and call your healthcare provider right away if you get movements you cannot stop or control, such as:

- lip smacking, chewing, or puckering up your mouth
- frowning or scowling
- sticking out your tongue
- blinking and moving your eyes
- shaking of your arms and legs

Your healthcare provider may decide not to continue treatment with GIMOTI if you develop signs or symptoms of tardive dyskinesia.

See the section "What are the possible side effects of GIMOTI?"for more information about side effects.

What is GIMOTI?

- GIMOTI is a prescription medicine used in adults to relieve the symptoms of slow stomach emptying in people with diabetes.
- GIMOTI is not recommendedfor use in people who:
  - have kidney or liver problems.
  - have been told that an enzyme in their body, called CYP2D6, breaks down (metabolizes) certain medicines in the body too slowly.
  - are also taking medicine called CYP2D6 inhibitors, which slows how fast the body breaks down (metabolizes) certain medicines.
- GIMOTI is not recommended for use in children.
- It is not known if GIMOTI is safe and effective in children.

Do not take GIMOTI if you:

- have a history of tardive dyskinesia or have a problem controlling your muscles and movements after taking GIMOTI or a medicine that works like GIMOTI.
- have stomach or intestine problems that could get worse with GIMOTI, such as bleeding, blockage, or a tear in the stomach or bowel wall.
- have a type of tumor that can cause high blood pressure, such as pheochromocytoma.
- have epilepsy (seizures). GIMOTI can increase your chance for seizures and make them worse.
- are allergic to metoclopramide. GIMOTI can cause serious allergic reactions. Stop taking GIMOTI right away and get emergency help if you have any of these symptoms:
  - swelling of your tongue, throat, lips, eyes, or face
  - trouble swallowing or breathing
  - skin rash, hives, sores in your mouth, or skin blisters

Before taking GIMOTI, tell your healthcare provider about all of your medical conditions, including if you:

- had problems controlling your muscle movements after taking any medicine.
- have Parkinson’s disease.
- have or had depression or mental illness.
- have kidney or liver disease.
- have heart failure or heart rhythm problems.
- have high blood pressure.
- drink alcohol.
- have diabetes. Your dose of insulin may need to be changed.
- are pregnant or plan to become pregnant. GIMOTI may harm your unborn baby if taken during the end of pregnancy. Talk to your healthcare provider if you become pregnant while taking GIMOTI.
- are breastfeeding or plan to breastfeed. GIMOTI can pass into your breast milk and may harm your baby. It is important that you tell your baby’s healthcare provider you are taking GIMOTI. You and your healthcare provider should decide if you will take GIMOTI or breastfeed.

Tell your healthcare provider about all the medicines you take, including prescription and over-the-counter medicines, vitamins, and herbal supplements.

GIMOTI may affect the way other medicines work and other medicines may affect how GIMOTI works.
Tell your healthcare provider before you start or stop other medicines.

Especially tell your healthcare provider if you take:

- another medicine that contains metoclopramide, such as metoclopramide tablets, metoclopramide injection, metoclopramide orally disintegrating tablets (ODT), or metoclopramide oral solution.
- an anti-psychotic medicine, used to treat mental illness such as schizophrenia.
- a medicine for Parkinson’s disease.
- a medicine for depression, especially a monoamine oxidase inhibitor (MAOI).
- insulin.
- medicines that can make you sleepy, such as anxiety medicines, sleep medicines, and narcotics.

If you are not sure if your medicine is one listed above, ask your healthcare provider or pharmacist.
Know the medicines you take. Keep a list of them to show your healthcare provider and pharmacist when you get a new medicine.

How should I take GIMOTI?

- Read the step-by-step Instructions for Use that come with your GIMOTI prescription.
- Take GIMOTI exactly as your healthcare provider tells you. Do not change your dose unless your healthcare provider tells you to.
- GIMOTI comes as a liquid in a glass bottle with a spray pump attached.
- You should not take medicines containing metoclopramide (including GIMOTI) for more than 12 weeks. If you require treatment for longer than 12 weeks, your healthcare provider should frequently monitor you for signs and symptoms of tardive dyskinesia.
- Take GIMOTI at least 30 minutes before each meal and at bedtime.
- If you are not certain that the spray entered the nose, skip the dose and take your next dose at your regular schedule time. Do not take an extra dose at the schedule time. If you miss a dose of GIMOTI, skip that dose and take your next dose at your regular scheduled time. Do not take an extra dose to make up for a missed dose.
- If you take too much GIMOTI, call your poison control center at 1-800-222-1222 or go to the nearest emergency room right away.
- Keep all follow-up visits with your healthcare provider as scheduled, so that your healthcare provider can see how you are responding to treatment with GIMOTI.

What should I avoid while taking GIMOTI?

- Do not drink alcohol while taking GIMOTI. Alcohol may make some side effects of GIMOTI worse, such as feeling sleepy.
- Do not drive, operate machinery, or do other dangerous activities until you know how GIMOTI affects you. GIMOTI may cause sleepiness or dizziness.

What are the possible side effects of GIMOTI?
GIMOTI can cause serious side effects, including:

- Tardive dyskinesia (abnormal muscle movements).
  See " What is the most important information I need to know about GIMOTI?"
- Other changes in muscle control and movement, such as:
  - Uncontrolled spasms of your face and neck muscles, or muscles of your body, arms, and legs (dystonia).These muscle spasms can cause abnormal movements and body positions and speech problems. These spasms usually start within the first 2 days of treatment. Rarely, these muscle spasms may cause trouble breathing. These spasms happen more often in adults less than 30 years of age and in those who took higher doses of metoclopramide.
  - Parkinsonism.Symptoms include slight shaking, body stiffness, and trouble moving or keeping your balance. If you already have Parkinson's Disease, your symptoms may become worse while you are taking GIMOTI.
  - Being unable to sit still or feeling you need to move your hands, feet, or body (akathisia).Symptoms can include feeling jittery, anxious, irritated, or unable to sleep (insomnia), feeling the need to walk around (pacing), and tapping your feet. Your healthcare provider may stop your treatment with GIMOTI if you develop these symptoms.
- Neuroleptic Malignant Syndrome (NMS).NMS is a very rare, but very serious condition that can happen with GIMOTI. NMS can cause death and must be treated in a hospital. Symptoms of NMS include: high fever, stiff muscles, problems thinking, very fast or uneven heartbeat, and increased sweating.
- Depression, thoughts about suicide, and suicide.Some people who take GIMOTI may become depressed, even if they have no history of depression. You may have thoughts about hurting or killing yourself. Some people who have taken metoclopramide have ended their own lives (suicide). Tell your healthcare provider right away if you have these feelings.
- High blood pressure.GIMOTI can cause your blood pressure to increase. Your healthcare provider may stop your treatment if GIMOTI causes your blood pressure to increase very fast.
- Too much body water.People who have certain liver problems or heart failure and take GIMOTI may hold too much water in their body (fluid retention). Tell your healthcare provider right away if you have sudden weight gain, or swelling of your hands, legs, or feet.
- Increased prolactin.Tell your healthcare provider if your menstrual periods stop or your breasts get larger and make milk. These symptoms go away when you stop taking GIMOTI.

Stop taking GIMOTI, call your healthcare provider and get medical help right away if you:

- have muscle movements you cannot stop or control
- have muscle movements that are new or unusual
- feel depressed or have thoughts about hurting or killing yourself
- have high fever, stiff muscles, problems thinking, very fast or uneven heartbeat, and increased sweating

The most common side effects of GIMOTI include:

- unpleasant taste
- headache
- tiredness

You may have more side effects the longer you take GIMOTI and the more GIMOTI you take.
You may still have side effects after stopping GIMOTI. You may have symptoms from stopping GIMOTI such as headaches and feeling dizzy or nervous.
Tell your healthcare provider about any side effect that bothers you or that does not go away. These are not all the possible side effects of GIMOTI. Call your doctor for medical advice about side effects. You may report side effects to FDA at 1-800-FDA-1088.

How should I store GIMOTI?

- Store GIMOTI at room temperature between 68°F to 77°F (20°C to 25°C).
- Throw away (discard) GIMOTI 4 weeks after opening even if the bottle contains unused medicine.

Keep GIMOTI and all medicines out of the reach of children.

General information about the safe and effective use of GIMOTI.
Medicines are sometimes prescribed for purposes other than those listed in a Medication Guide. Do not use GIMOTI for a condition for which it was not prescribed. Do not give GIMOTI to other people, even if they have the same symptoms that you have. It may harm them.
You can ask your pharmacist or healthcare provider for information about GIMOTI that is written for health professionals.

What are the ingredients in GIMOTI?
Active ingredient:metoclopramide
Inactive ingredients:benzalkonium chloride, citric acid monohydrate, edetate disodium dihydrate, purified water, sodium citrate dihydrate, sorbitol.
Manufactured for Evoke Pharma, Inc. by Patheon, a Division of Thermo Fisher.
GIMOTI is a trademark of Evoke Pharma.©2020 Evoke Pharma, Inc. All rights reserved.
For more information, go to www.evokepharma.com or call 1-833-4-GIMOTI (1-833-444-6684).

This Medication Guide has been approved by the U.S. Food and Drug Administration

Revised: February 2026

Instructions for Use

GIMOTI™ (jye-MOH-tee) (phonetic spelling)

(metoclopramide)
nasal spray

Read this Instructions for Use before you start using GIMOTI nasal spray and each time you get a refill. This information does not take the place of talking to your healthcare provider about your medical condition or your treatment.

Important information:

- GIMOTI is for use in your nose only.
- The GIMOTI nasal spray bottle has enough medicine for 4 weeks of treatment if taken 4 times each day.
- 1 dose is 1 spray in 1 nostril.
- Your GIMOTI nasal spray bottle must be primed:
  - before you use it for the first time,
  - when the nasal spray has not been used for 2 weeks .
- Store the GIMOTI nasal spray at room temperature between 68°F to 77°F (20°C to 25°C).
- Throw away (discard) the GIMOTI nasal spray 4 weeks after opening even if the bottle contains unused medicine.
- Keep out of the reach of children.

Parts of your GIMOTI bottle

Steps to use GIMOTI

1. Uncap the GIMOTI nasal spray bottle

- Remove the cap from the spray nozzle by pulling straight up.

2. Prime the GIMOTI nasal spray bottle

- Remove the safety clip from the spray pump.
- Place your index finger and middle finger on each side of the finger flange and your thumb on the bottom of the glass bottle.
- Turn the spray nozzle away from your face, keeping the bottle upright. Do notspray into your eyes.

- Press down firmly and release 10 times on the finger flange until a spray appears from the spray nozzle. You may not see a spray the first few times you press down. After pressing down and releasing a spray 10 times, the GIMOTI nasal spray will be primed and ready to use.

If you are not able to press and release 10 sprays from the GIMOTI nasal spray, call your healthcare provider or pharmacist.

The GIMOTI nasal spray bottle is now ready for use.

3. Using the GIMOTI nasal spray

- Place the spray nozzle tip under one of your nostrils. Tilt your head slightly forward so the tip of the spray nozzle is aimed away from the center of your nose.
- Close the other nostril with your other index finger. Move the spray pump up so the tip of the nozzle is in your nostril.
- Press down firmly on the finger flange until it stops moving to deliver a full dose.
- Release the finger flange and breathe in gently through the open nostril.
- Remove the spray pump nozzle tip from your nostril and breathe out slowly through your mouth.
- After use, wipe the spray nozzle with a clean tissue. Place the cap on the spray nozzle by pushing straight down. Place the safety clip back onto the spray pump.

Cleaning the spray pump nozzle

If the spray pump nozzle becomes clogged, remove it for cleaning by grasping the base of the spray nozzle and pulling up.

Soak the spray nozzle in warm water and rinse. Do nottry to unblock the spray nozzle by inserting a pin or other sharp object because this will damage the spray nozzle .

Dry the spray nozzle at room temperature. When the spray nozzle is dry, place the dry spray nozzle back on the GIMOTI bottle.

Disposal instructions

The used GIMOTI nasal spray may be thrown away (discarded) in the household trash.

Manufactured for Evoke Pharma, Inc. by Patheon, a Division of Thermo Fisher.

GIMOTI is a trademark of Evoke Pharma.©2020 Evoke Pharma, Inc. All rights reserved.

For more information, go to www.evokepharma.com or call 1-833-4-GIMOTI (1-833-444-6684).

These Instructions for Use have been approved by the U.S. Food and Drug Administration
Approved: June 2020

PRINCIPAL DISPLAY PANEL - 9.8 mL Bottle Carton

NDC 72089-307-15

Gimoti™
(metoclopramide)
nasal spray

15 mg
per spray

FOR NASAL USE ONLY

Rx Only

Net Content 9.8 mL
112 metered sprays

EVOKE
PHARMA